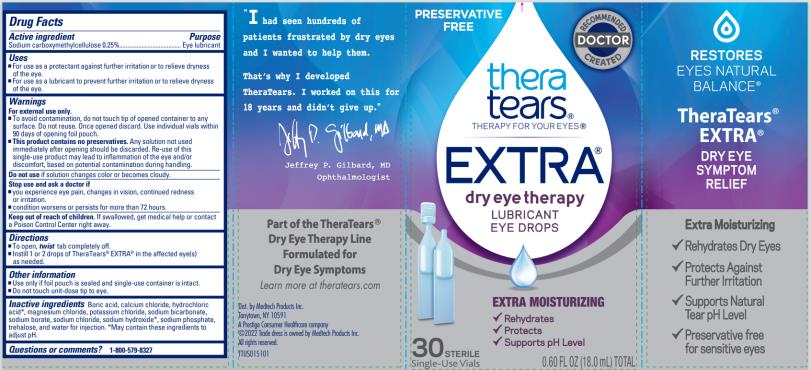 DRUG LABEL: TheraTears Extra
NDC: 58790-010 | Form: SOLUTION/ DROPS
Manufacturer: MEDTECH PRODUCTS INC
Category: otc | Type: HUMAN OTC DRUG LABEL
Date: 20241213

ACTIVE INGREDIENTS: Carboxymethylcellulose Sodium, Unspecified 2.5 mg/1 mL
INACTIVE INGREDIENTS: Boric Acid; calcium chloride; hydrochloric acid; magnesium chloride; potassium chloride; sodium bicarbonate; sodium borate; sodium chloride; sodium hydroxide; sodium phosphate; trehalose; water

TheraTears Extra PF 58790-010

Drug Facts

Active ingredient

Sodium carboxymethylcellulose 0.25%

Purpose

Eye lubricant

Uses

- For use as a protectant against further irritation or to relieve dryness of the eye.
- For use as a lubricant to prevent further irritation or to relieve dryness of the eye.

Warnings

For external use only

- To avoid contamination, do not touch tip of opened container to any surface.
  Do not reuse. Once opened discard. Use individual vials within 90 days of opening foil pouch.
- This product contains no preservatives. Any solution not used immediately after opening should he discarded. Re-use of this single-use product may lead to inflammation of the eye and/or discomfort, based on potential contamination during handling.

Do not use

- if solution changes color or becomes cloudy.

Stop use and ask a doctor if

- you experience eye pain, changes in vision, continued redness or irritation.
- condition worsens or persists for more than 72 hours.

Keep out of reach of children.

If swallowed, get medical help or contact a Poison Control Center right away.

Directions

- To open, twist tab completely off.
- Instill 1 or 2 drops of TheraTears® EXTRA® in the affected eye(s) as needed

Other information

- Use only if foil pouch is sealed and single-use container is intact.
- Do not touch unit-dose tip to eye.

Inactive ingredients

Boric acid, calcium chloride, hydrochloric acid*, magnesium chloride, potassium chloride, sodium bicarbonate, sodium borate, sodium chloride, sodium hydroxide*, sodium phosphate, trehalose, and water for injection. *May contain these ingredients to adjust pH.

Questions or comments?

1-800-579-8327

Principal Display Panel Text for Carton Label:

PRESERVATIVE

FREE

RECOMMENDED

DOCTOR

CREATED

thera

tears®

THERAPY FOR YOUR EYES®

EXTRA®

dry eye therapy

LUBRICANT

EYE DROPS

EXTRA MOISTURIZING

√ Rehydrates

√ Protects

√ Supports pH Level

30 STERILE

Single-Use Vials 0.60 FL OZ (18.0 mL) TOTAL